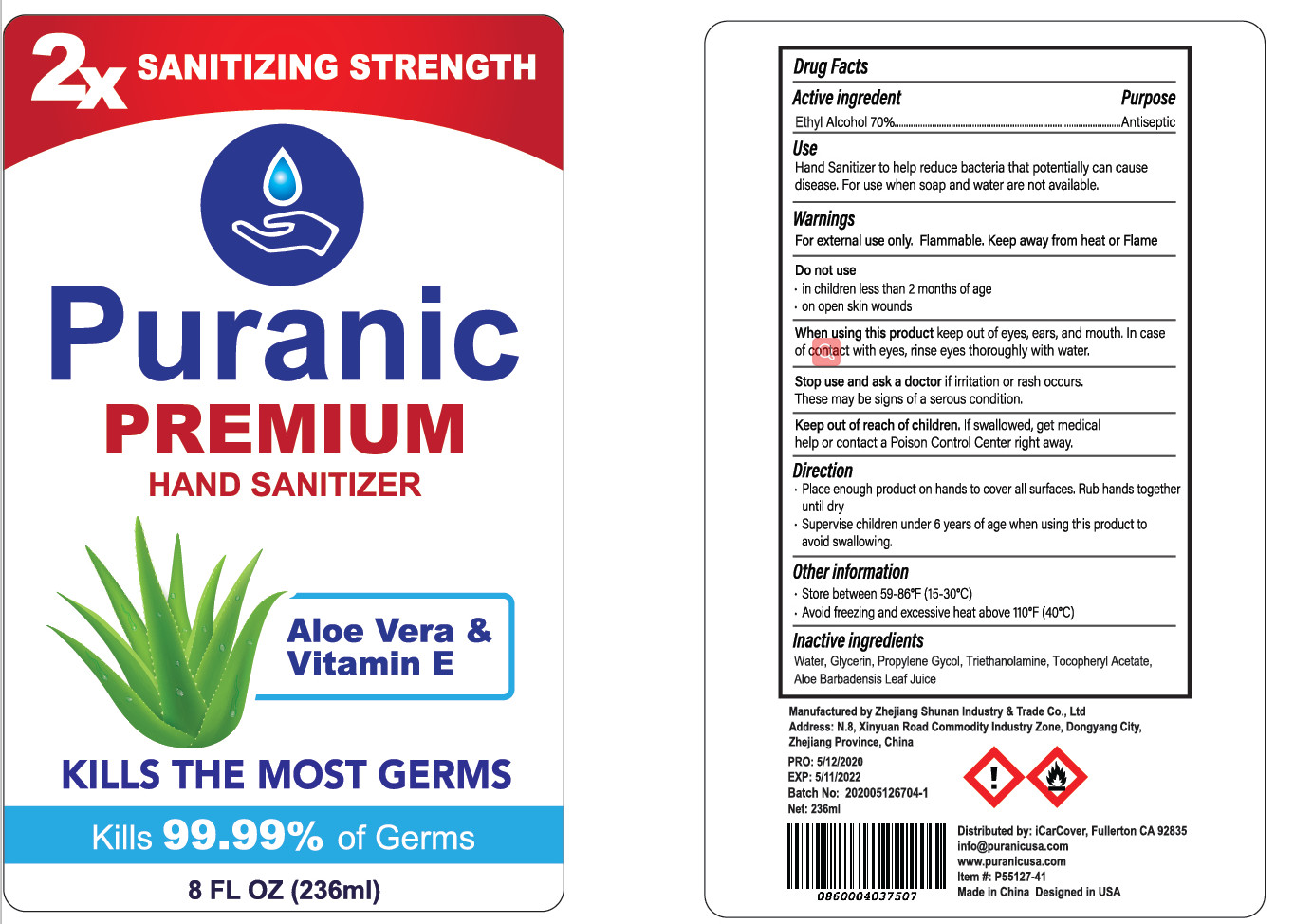 DRUG LABEL: Hand Sanitizer
NDC: 75556-002 | Form: LIQUID
Manufacturer: ZHEJIANG SHUNAN INDUSTRY&TRADE CO.,LTD
Category: otc | Type: HUMAN OTC DRUG LABEL
Date: 20200519

ACTIVE INGREDIENTS: ALCOHOL 165.2 mL/236 mL
INACTIVE INGREDIENTS: .ALPHA.-TOCOPHEROL; CARBOMER HOMOPOLYMER, UNSPECIFIED TYPE; WATER; ALOE

DOSAGE AND ADMINISTRATION

Store between 59-86°F (15-30°C),Avoid feezing and excessive heat above 10°F (40°C)

INACTIVE INGREDIENT

Water ，carbomer , Aloe Vera， Vitamin E

INDICATIONS AND USAGE

Place enough product on hands to cover all surfaces. Rub hands together until dry

ACTIVE INGREDIENT

Ethyl Alcohol

keep out of reach of children

PURPOSE

Disinfection
Sterilization
No Rinseing

WARNINGS

For extermal use only. Flammable. Keep away from heat or Fame.